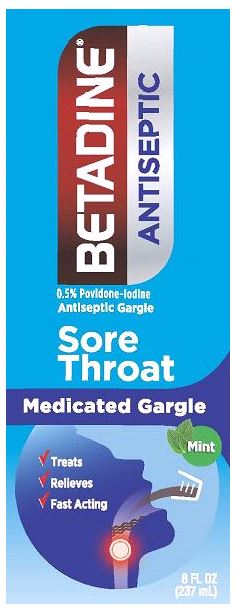 DRUG LABEL: Betadine Gargle
NDC: 67618-181 | Form: SOLUTION
Manufacturer: Atlantis Consumer Healthcare, Inc.
Category: otc | Type: HUMAN OTC DRUG LABEL
Date: 20260121

ACTIVE INGREDIENTS: POVIDONE-IODINE .05 mg/1 mL
INACTIVE INGREDIENTS: GLYCERIN; PROPYLENE GLYCOL; WATER; SACCHARIN SODIUM; SODIUM HYDROXIDE; ANHYDROUS CITRIC ACID

BETADINE® Sore Throat Gargle
0.5% Povidone-iodine

Drug Facts

Active ingredient

Povidone-iodine, 0.5%(0.05% available iodine)

Purpose

Antiseptic

Uses

- For the temporary relief of occasional sore throat

Warnings

SoreThroat Warning: Severe or persistent sore throat or sore throataccompanied by high fever, headache, nausea, and vomiting may be serious.Consult doctor promptly. Do not use more than 2 days or administerto children under 3 years of age unless directed by a doctor.

Do not use this product

- for more than 7 days unless directed by a dentist or doctor
- if you are allergic to povidone-iodine or any other ingredientsin this product
- if you have any thyroid conditions

When using this product

- do not get into eyes. If contact occurs, rinse eyes thoroughlywith water. If irritation persists, consult a doctor
- do not swallow
- do not use with hydrogen peroxide

Stop use and ask a doctor if

- symptoms do not improve in 7 days
- irritation, pain, or redness persists or worsens
- swelling, rash, or fever develops

PREGNANCY OR BREAST FEEDING

If pregnant or breast-feeding, ask a health professional before use.

Keep out of reach of children. In case more than used for gargling is accidentally swallowed, getmedical help or contact a Poison Control Center right away.

Directions

DO NOT SWALLOW
Adults andchildren 12 years and older:

- Gargle with 10 ml full strength for 30 seconds, then spitout
- Use only with dosing cup provided
- Use up to 4 times daily

Children under 12: Do not use.

Other information

- store at 25⁰C (77⁰F); excursions permitted between 15⁰-30⁰C(59⁰-86⁰F)
- may stain clothing or dental work
- avoid contact with jewelry, especially silver

Inactive ingredients

citric acid,flavor, glycerin, propylene glycol, purified water, saccharin sodium,sodium hydroxide

Dist. by: Avrio Health L.P.Stamford, CT 06901-3431
305586-0E

PACKAGE LABEL

BetadineGargle Carton
NDC: 67618-181-08